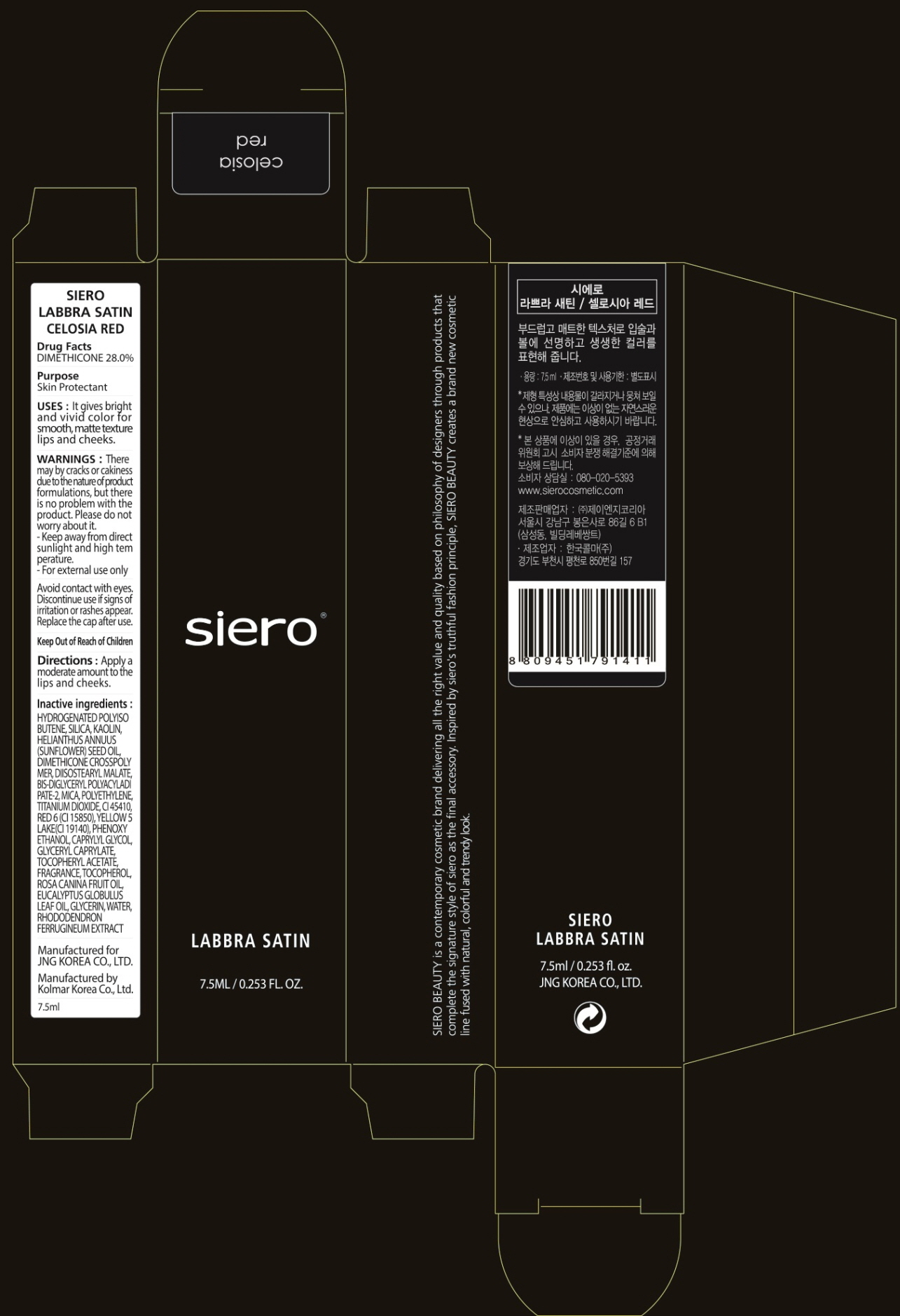 DRUG LABEL: SIERO LABBRA SATIN CELOSIA RED
NDC: 71472-180 | Form: GEL
Manufacturer: JNG KOREA CO.,LTD.
Category: otc | Type: HUMAN OTC DRUG LABEL
Date: 20170629

ACTIVE INGREDIENTS: DIMETHICONE 2.1 g/7.5 mL
INACTIVE INGREDIENTS: KAOLIN

ACTIVE INGREDIENT

Active ingredients: DIMETHICONE 28.0%

INACTIVE INGREDIENT

Inactive ingredients: HYDROGENATED POLYISOBUTENE, SILICA, KAOLIN, HELIANTHUS ANNUUS (SUNFLOWER) SEED OIL, DIMETHICONE CROSSPOLYMER, DIISOSTEARYL MALATE, BIS-DIGLYCERYL POLYACYLADIPATE-2, MICA, POLYETHYLENE, TITANIUM DIOXIDE, CI 45410, RED 6 (CI 15850), YELLOW 5 LAKE(CI 19140), PHENOXYETHANOL, CAPRYLYL GLYCOL, GLYCERYL CAPRYLATE, TOCOPHERYL ACETATE, FRAGRANCE, TOCOPHEROL, ROSA CANINA FRUIT OIL, EUCALYPTUS GLOBULUS LEAF OIL, GLYCERIN, WATER, RHODODENDRON FERRUGINEUM EXTRACT

PURPOSE

Purpose: Skin Protectant

WARNINGS

Warnings: - There may by cracks or cakiness due to the nature of product formulations, but there is no problem with the product. Please do not worry about it. - Keep away from direct sunlight and high temperature. - For external use only Avoid contact with eyes. Discontinue use if signs of irritation or rashes appear. Replace the cap after use.

KEEP OUT OF REACH OF CHILDREN

Uses

Uses: It gives bright and vivid color for smooth, matte texture lips and cheeks.

Directions

Directions: Apply a moderate amount to the lips and cheeks.